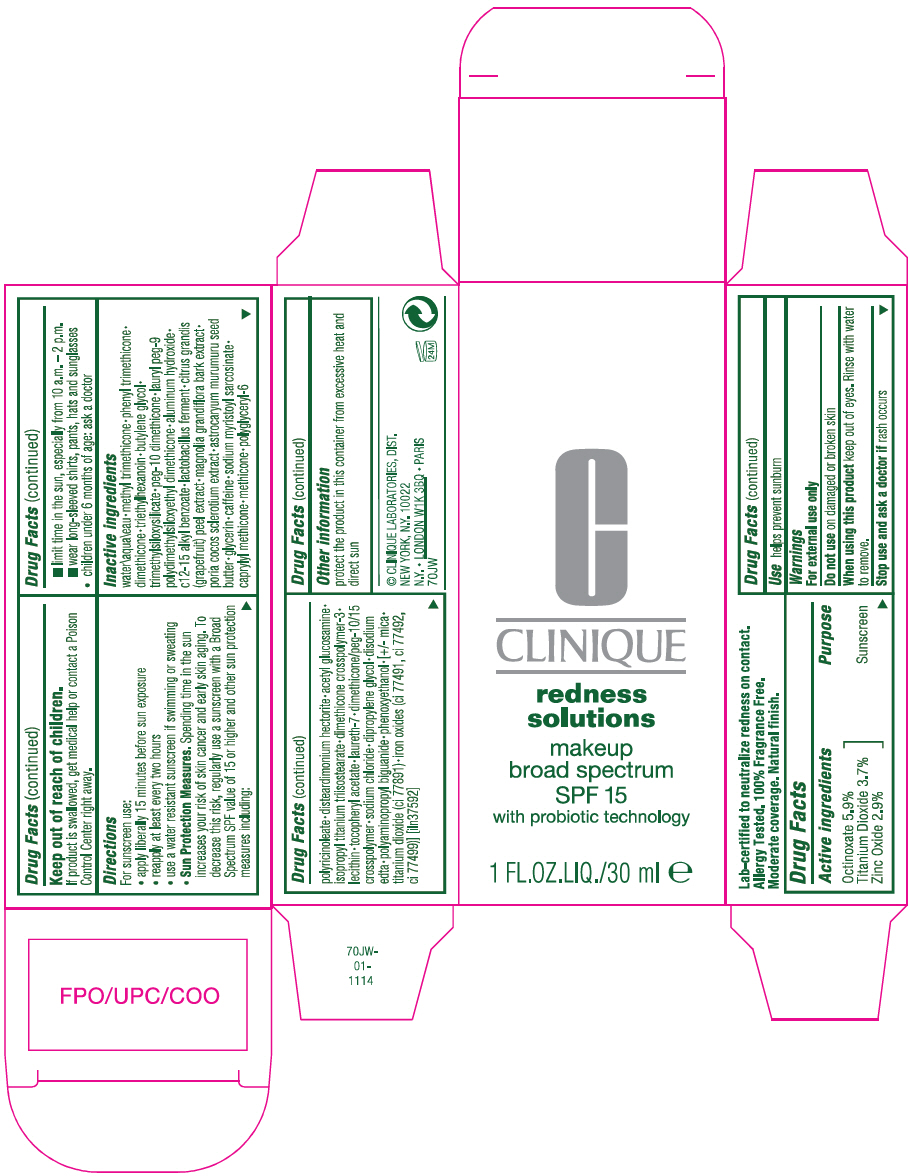 DRUG LABEL: REDNESS solutions MAKEUP BROAD SPECTRUM SPF 15 WITH PROBIOTIC TECHNOLOGY
NDC: 49527-070 | Form: LOTION
Manufacturer: CLINIQUE LABORATORIES LLC
Category: otc | Type: HUMAN OTC DRUG LABEL
Date: 20231013

ACTIVE INGREDIENTS: OCTINOXATE 59 mg/1 mL; TITANIUM DIOXIDE 37 mg/1 mL; ZINC OXIDE 29 mg/1 mL
INACTIVE INGREDIENTS: METHYL TRIMETHICONE; WATER; PHENYL TRIMETHICONE; DIMETHICONE; TRIETHYLHEXANOIN; BUTYLENE GLYCOL; PEG-10 DIMETHICONE (600 CST); LAURYL PEG-9 POLYDIMETHYLSILOXYETHYL DIMETHICONE; ALUMINUM HYDROXIDE; ALKYL (C12-15) BENZOATE; LIMOSILACTOBACILLUS REUTERI; GRAPEFRUIT; ASTROCARYUM MURUMURU SEED BUTTER; GLYCERIN; CAFFEINE; SODIUM MYRISTOYL SARCOSINATE; CAPRYLYL TRISILOXANE; METHICONE (20 CST); DISTEARDIMONIUM HECTORITE; N-ACETYLGLUCOSAMINE; ISOPROPYL TITANIUM TRIISOSTEARATE; LAURETH-7; SODIUM CHLORIDE; DIPROPYLENE GLYCOL; EDETATE DISODIUM ANHYDROUS; PHENOXYETHANOL; MICA; FERRIC OXIDE RED; FERRIC OXIDE YELLOW; FERROSOFERRIC OXIDE

REDNESS SOLUTIONS MAKEUP BROAD SPECTRUM SPF 15 WITH PROBIOTIC TECHNOLOGY

Drug Facts

Active ingredients

Octinoxate 5.9%
Titanium Dioxide 3.7%
Zinc Oxide 2.9%

Purpose

Sunscreen

Use

helps prevent sunburn

Warnings

For external use only

Do not use on damaged or broken skin

When using this product keep out of eyes. Rinse with water to remove.

Stop use and ask a doctor if rash occurs

Keep out of reach of children.

If product is swallowed, get medical help or contact a Poison Control Center right away.

Directions

For sunscreen use:

- apply liberally 15 minutes before sun exposure
- reapply at least every two hours
- use a water resistant sunscreen if swimming or sweating
- Sun Protection Measures. Spending time in the sun increases your risk of skin cancer and early skin aging. To decrease this risk, regularly use a sunscreen with a Broad Spectrum SPF value of 15 or higher and other sun protection measures including:
  - limit time in the sun, especially from 10 a.m. – 2 p.m.
  - wear long-sleeved shirts, pants, hats and sunglasses
- children under 6 months of age: ask a doctor

Inactive ingredients

water\aqua\eau • methyl trimethicone • phenyl trimethicone • dimethicone • triethylhexanoin • butylene glycol • trimethylsiloxysilicate • peg-10 dimethicone • lauryl peg-9 polydimethylsiloxyethyl dimethicone • aluminum hydroxide • c12-15 alkyl benzoate • lactobacillus ferment • citrus grandis (grapefruit) peel extract • magnolia grandiflora bark extract • poria cocos sclerotium extract • astrocaryum murumuru seed butter • glycerin • caffeine • sodium myristoyl sarcosinate • caprylyl methicone • methicone • polyglyceryl-6 polyricinoleate • disteardimonium hectorite • acetyl glucosamine • isopropyl titanium triisostearate • dimethicone crosspolymer-3 • lecithin • tocopheryl acetate • laureth-7 • dimethicone/peg-10/15 crosspolymer • sodium chloride • dipropylene glycol • disodium edta • polyaminopropyl biguanide • phenoxyethanol • [+/- mica • titanium dioxide (ci 77891) • iron oxides (ci 77491, ci 77492, ci 77499)] [iln37592]

Other information

protect the product in this container from excessive heat and direct sun

PRINCIPAL DISPLAY PANEL - 30 ml Bottle Carton

CLINIQUE

redness
solutions

makeup
broad spectrum
SPF 15
with probiotic technology

1 FL.OZ.LIQ./30 ml e